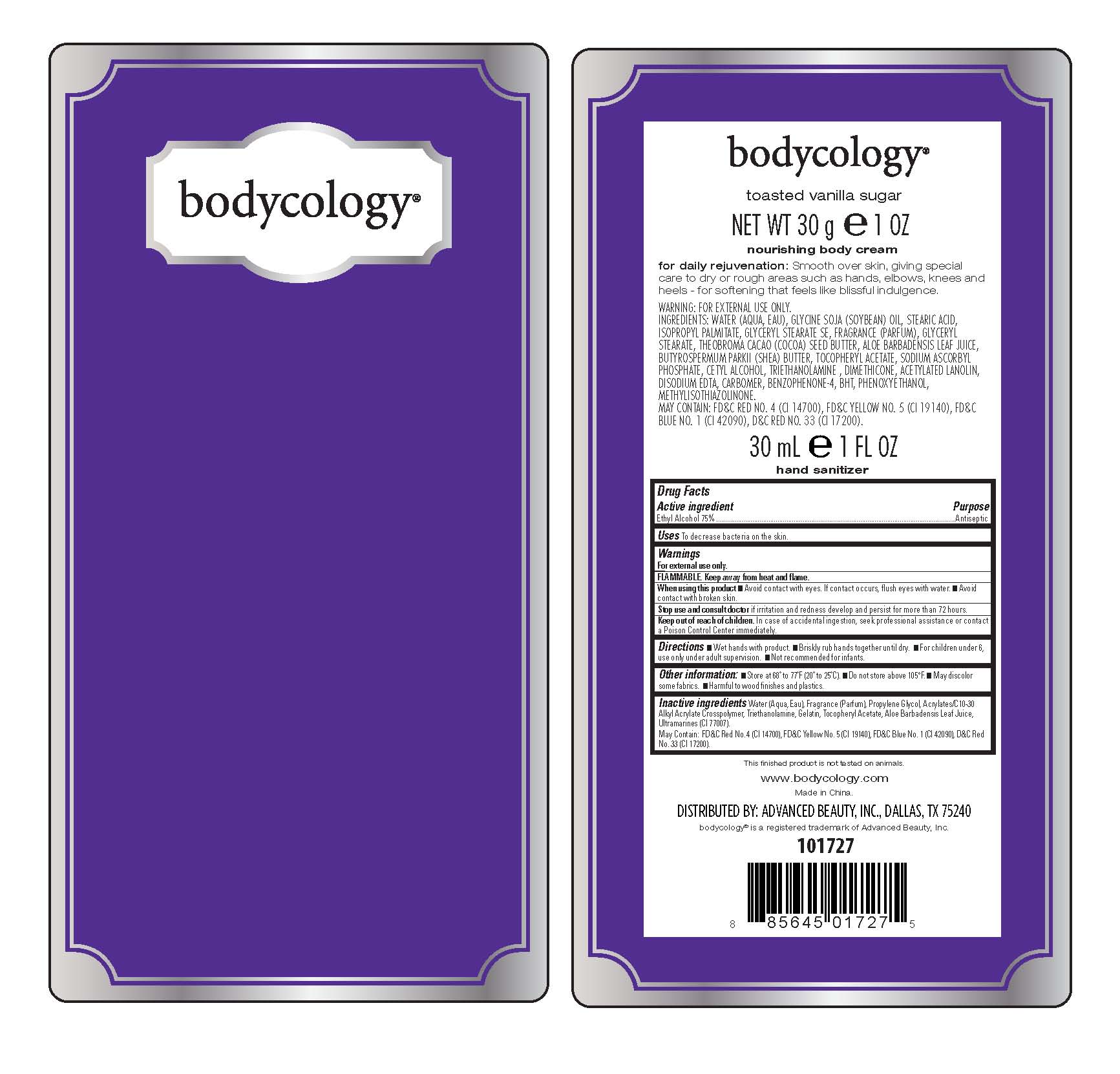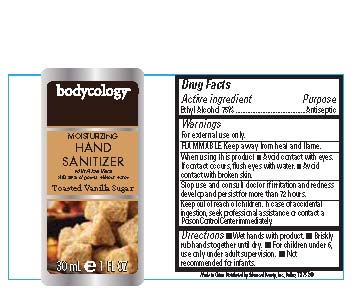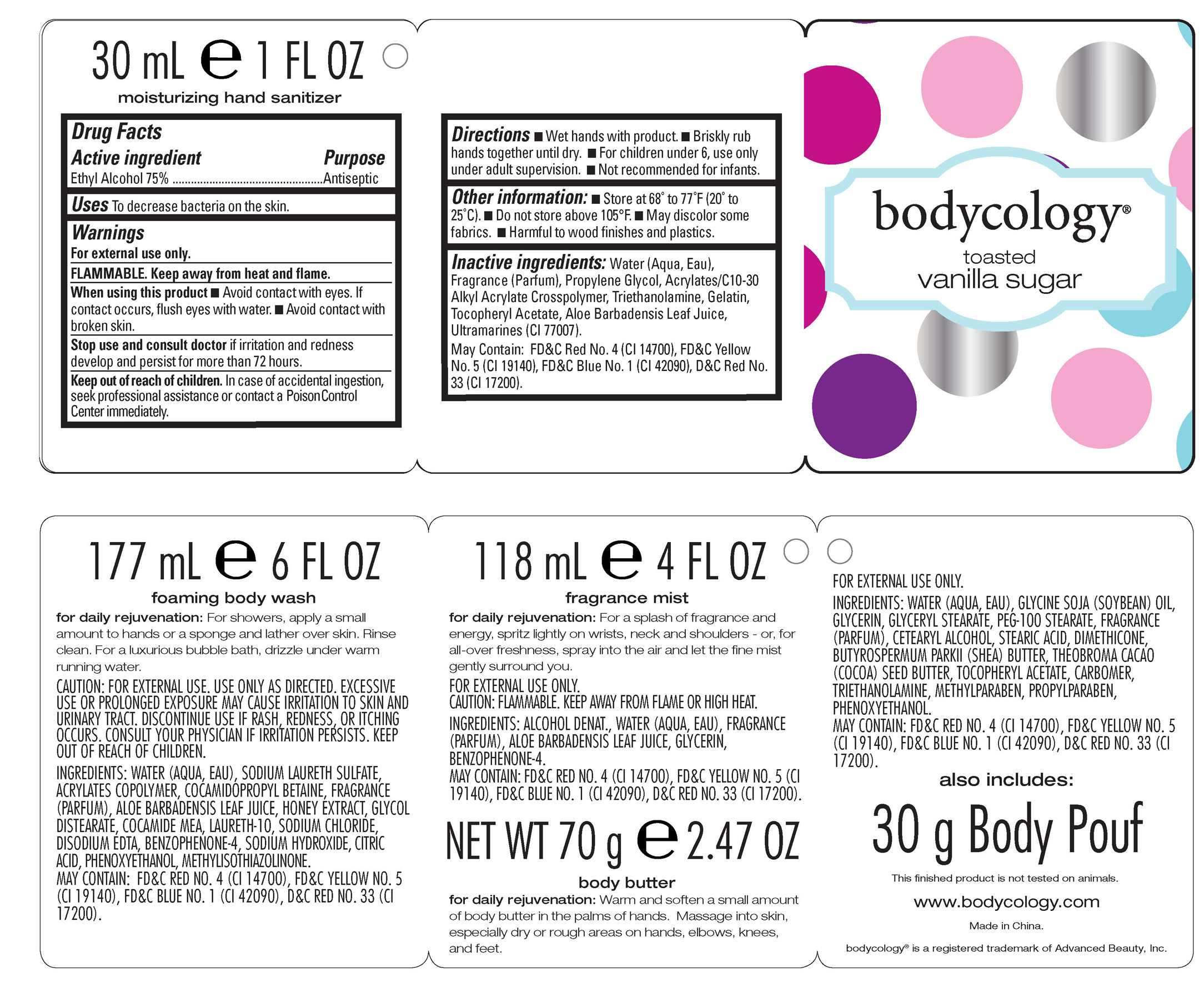 DRUG LABEL: Toasted Vanilla Sugar Hand Sanitizer 
NDC: 51345-105 | Form: LIQUID
Manufacturer: Advanced Beauty Systems, Inc.
Category: otc | Type: HUMAN OTC DRUG LABEL
Date: 20120629

ACTIVE INGREDIENTS: ALCOHOL 22.5 mL/30 mL
INACTIVE INGREDIENTS: PROPYLENE GLYCOL; TROLAMINE; GELATIN; ALOE VERA LEAF; FD&C RED NO. 4; FD&C YELLOW NO. 5; FD&C BLUE NO. 1; D&C RED NO. 33

Toasted Vanilla Sugar Hand Sanitizer

Active Ingredient purpose

Ethyl Alcohol 75% Antiseptic

PURPOSE

Uses: to decrease bacteria on the skin.

Keep out of reach of children.

Stop use and consult a doctor if irritation and redness develop and persist for more than 72 hours.

Warnings: For external use only.
Flammable. Keep away from heat and flame.
When using this product: Avoid contact with eyes. If contact occurs, flush eyes with water. Avoid contact with broken skin.
In case of accidental ingestion, seek professional assistance or contact a Poison Control Center immediately.

DOSAGE AND ADMINISTRATION

Directions: Wet hands with product.

Briskly rub hands together until dry.

For children under 6, use only under adult supervision.

Not recommended for infants.

INACTIVE INGREDIENT

Inactive ingredients: Water (aqua, eau), fragrance (parfum), Propylene Glycol, Acrylates/C10-30 Alkyl Acrylate Crosspolymer
triethanolamine, Gelatin, Tocopheryl Acetate, Aloe Barbadensis Leaf Juice, Ultramarines (CI77007)
May contain: FD C Red No.4(CI 14700), FD C Yellow No. 5 (CI 19140), FD C Blue No.1 (CI 42090), D C Red No 33(CI 17200)

PACKAGE LABEL

Bodycology

Moisturizing

Hand Sanitizer

with Aloe Vera
kills 99% of germs without water
Toasted Vanilla Sugar
30 mL 1 Fl Oz